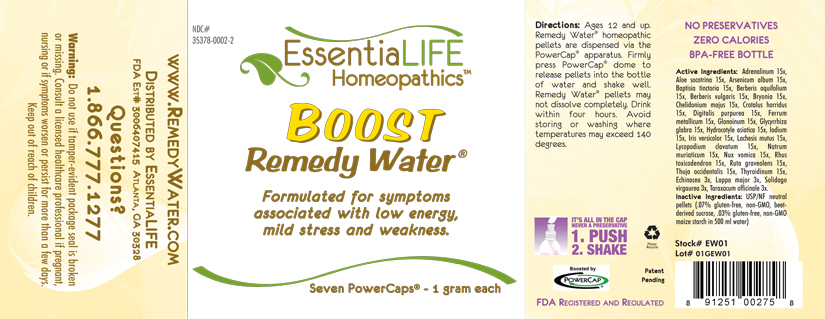 DRUG LABEL: Boost Remedy Water 
NDC: 35378-0002 | Form: PELLET
Manufacturer: Georgetown Health, LLC DBA EssentiaLife
Category: homeopathic | Type: HUMAN OTC DRUG LABEL
Date: 20120610

ACTIVE INGREDIENTS: Epinephrine 15 [hp_X]/1 mg; Aloe 15 [hp_X]/1 mg; Arsenic Trioxide 15 [hp_X]/1 mg; Baptisia Tinctoria Root 15 [hp_X]/1 mg; Mahonia Aquifolium Root Bark 15 [hp_X]/1 mg; Berberis Vulgaris Root Bark 15 [hp_X]/1 mg; Bryonia Alba Root 15 [hp_X]/1 mg; Chelidonium Majus 15 [hp_X]/1 mg; Crotalus Horridus Horridus Venom 15 [hp_X]/1 mg; Digitalis 15 [hp_X]/1 mg; Iron 15 [hp_X]/1 mg; Nitroglycerin 15 [hp_X]/1 mg; Glycyrrhiza Glabra 15 [hp_X]/1 mg; Centella Asiatica 15 [hp_X]/1 mg; Iodine 15 [hp_X]/1 mg; Iris Versicolor Root 15 [hp_X]/1 mg; Lachesis Muta Venom 15 [hp_X]/1 mg; Lycopodium Clavatum Spore 15 [hp_X]/1 mg; Sodium Chloride 15 [hp_X]/1 mg; Strychnos Nux-vomica Seed 15 [hp_X]/1 mg; Toxicodendron Pubescens Leaf 15 [hp_X]/1 mg; Ruta Graveolens Flowering Top 15 [hp_X]/1 mg; Thuja Occidentalis Leafy Twig 15 [hp_X]/1 mg; Thyroid, Unspecified 15 [hp_X]/1 mg; Echinacea, Unspecified 3 [hp_X]/1 mg; Arctium Lappa Root 3 [hp_X]/1 mg; Solidago Virgaurea Flowering Top 3 [hp_X]/1 mg; Taraxacum Officinale 3 [hp_X]/1 mg
INACTIVE INGREDIENTS: Starch, Corn; Sucrose

Boost Remedy Water®

Active Ingredients

Adrenalinum | 15x
Aloe socotrina | 15x
Arsenicum album | 15x
Baptisia tinctoria | 15x
Berberis aquifolium | 15x
Berberis vulgaris | 15x
Bryonia | 15x
Chelidonium majus | 15x
Crotalus horridus | 15x
Digitalis purpurea | 15x
Ferrum metallicum | 15x
Glonoinum | 15x
Glycyrrhiza glabra | 15x
Hydrocotyle asiatica | 15x
Iodium | 15x
Iris versicolor | 15x
Lachesis mutus | 15x
Lycopodium clavatum | 15x
Natrum muriaticum | 15x
Nux vomica | 15x
Rhus toxicodendron | 15x
Ruta graveolens | 15x
Thuja occidentalis | 15x
Thyroidinum | 15x
Echinacea | 3x
Lappa major | 3x
Solidago virgaurea | 3x
Taraxacum officinale | 3x

Purpose

Formulated for symptoms associated with low energy, mild stress and weakness.

Uses

Formulated for symptoms associated with low energy, mild stress and weakness.

Warnings

Do not use if tamper-evident package seal is broken or missing. Consult a licensed healthcare professional if pregnant, nursing or if symptoms worsen or persist for more than a few days. Keep out of reach of children.

Directions

Ages 12 and up. Remedy Water® homepathic pellets are dispersed via the PowerCap® apparatus. Firmly press PowerCap® dome to release pellets into the bottle of water and shake well. Remedy Water® pellets may not dissolve completely. Drink within four hours. Avoid storing or washing where temperatures may exceed 140 degrees.

Inactive Ingredients

USP/NF neutral pellets (.07% gluten-free, non-GMO, beet-derived sucrose, .03% gluten-free, non-GMO maize starch in 500 ml water)

Other Information

Avoid storing where temperatures may exceed 140 degrees.

Questions?

1.866.777.1277
www.RemedyWater.com

PRINCIPAL DISPLAY PANEL

NDC# 35378-0002-2

EssentiaLIFE Homeopathics™

Boost Remedy Water®

Formulated for symptoms associated with low energy, mild stress and weakness.

Seven PowerCaps® - 1 gram each

Directions: Ages 12 and up. Remedy Water® homepathic pellets are dispersed via the PowerCap® apparatus. Firmly press PowerCap® dome to release pellets into the bottle of water and shake well. Remedy Water® pellets may not dissolve completely. Drink within four hours. Avoid storing or washing where temperatures may exceed 140 degrees.

IT'S ALL IN THE CAP
NEVER A PRESERVATIVE
1. PUSH
2. SHAKE

Please Recyle

Patent Pending

Boosted by PowerCap®

FDA Registered and Regulated

NO PRESERVATIVES
ZERO CALORIES
BPA-FREE BOTTLE

Active Ingredients: Adrenalinum 15x, Aloe socotrina 15x, Arsenicum album 15x, Baptisia tinctoria 15x, Berberis aquifolium 15x, Berberis vulgaris 15x, Bryonia 15x, Chelidonium majus 15x, Crotalus horridus 15x, Digitalis purpurea 15x, Ferrum metallicum 15x, Glonoinum 15x, Glycyrrhiza glabra 15x, Hydrocotyle asiatica 15x, Iodium 15x, Iris versicolor 15x, Lachesis mutus 15x, Lycopodium clavatum 15x, Natrum muriaticum 15x, Nux vomica 15x, Rhus toxicodendron 15x, Ruta graveolens15x, Thuja occidentalis 15x, Thyroidinum 15x, Echinacea 3x, Lappa major 3x, Solidago virgaurea 3x, Taraxacum officinale 3x.

Inactive ingredients: USP/NF neutral pellets (.07% gluten-free, non-GMO, beet-derived sucrose, .03% gluten-free, non-GMO maize starch in 500 ml water)

Stock# EW01

Lot# 01GEW01

www.RemedyWater.com

Distributed by EssentiaLIFE

FDA Est# 3006407415 Atlanta, GA 30328

Questions?

1.866.777.1277

Warning: Do not use if tamper-evident package seal is broken or missing. Consult a licensed healthcare professional if pregnant, nursing or if symptoms worsen or persist for more than a few days. Keep out of reach of children.